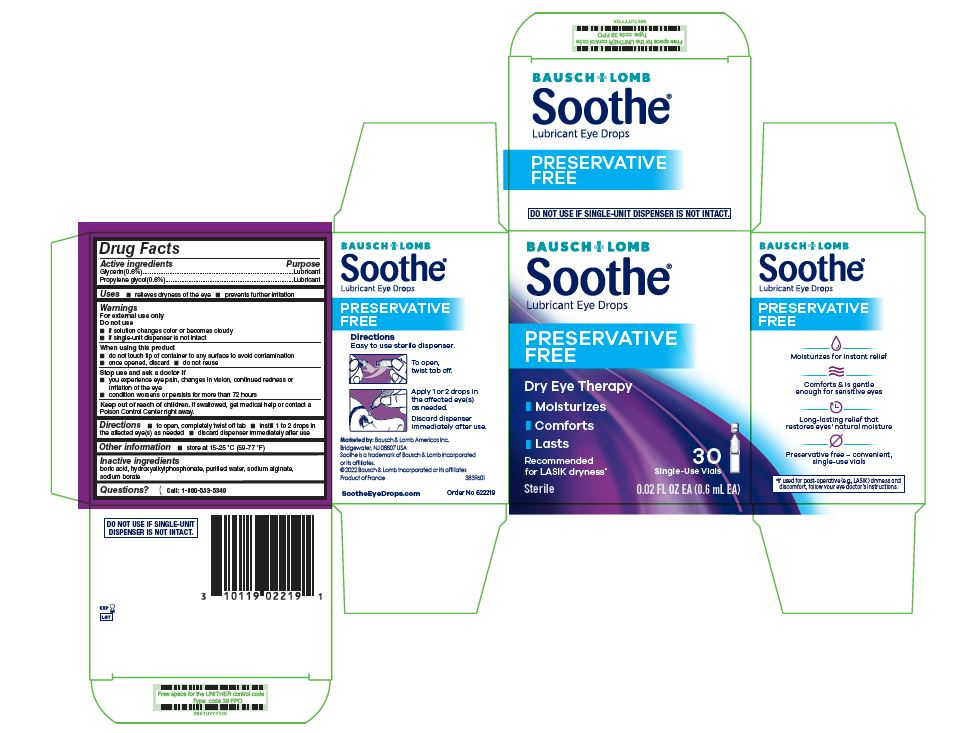 DRUG LABEL: Soothe
NDC: 24208-495 | Form: SOLUTION/ DROPS
Manufacturer: Bausch & Lomb Incorporated
Category: otc | Type: HUMAN OTC DRUG LABEL
Date: 20240920

ACTIVE INGREDIENTS: GLYCERIN 6 mg/1 mL; PROPYLENE GLYCOL 6 mg/1 mL
INACTIVE INGREDIENTS: BORIC ACID; WATER; SODIUM ALGINATE; SODIUM BORATE

Soothe Preservative Free Drug Facts

Active ingredients

Glycerin (0.6%)

Propylene glycol (0.6%)

Purpose

Lubricant

Lubricant

Uses

- relieves dryness of the eye
- prevents further irritation

Warnings

For external use only
Do not use

- if solution changes color or becomes cloudy
- if single-unit dispenser is not intact

When using this product

- do not touch tip of container to any surface to avoid contamination
- once opened, discard
- do not reuse

Stop use and ask a doctor if

- you experience eye pain, changes in vision, continued redness or irritation of the eye
- condition worsens or persists for more than 72 hours

Keep out of reach of children.

If swallowed, get medical help or contact a Poison Control Center right away.

Directions

- to open, completely twist off tab
- instill 1 to 2 drops in the affected eye(s) as needed
- discard dispenser immediately after use

Other information

- store at 15 – 25 °C (59 – 77 °F)

Inactive ingredients

boric acid, hydroxyalkylphosphonate, purified water, sodium alginate, sodium borate

Questions?

[phone icon] Call: 1-800-553-5340

Marketed by:
Bausch & Lomb Americas Inc.
Bridgewater, NJ 08807 USA

Soothe is a trademark of|
Bausch & Lomb Incorporated
or its affiliates.

© 2022 Bausch & Lomb
Incorporated or its affiliates
Product of France

Package/Label Principal Display Panel

Bausch & Lomb
Soothe®

Lubricant Eye Drops

PRESERVATIVE FREE

Dry Eye Therapy

- Moisturizes
- Comforts
- Lasts
- Recommended
  for LASIK dryness*
- 30 Single-Use Vials

Sterile 0.02 FL OZ EA (0.6 mL EA)

3839601

SootheEyeDrops.com

Order No. 622219